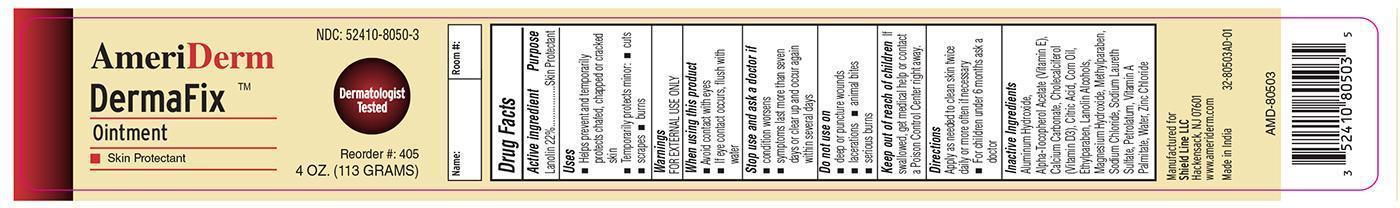 DRUG LABEL: AmeriDerm
NDC: 52410-8050 | Form: OINTMENT
Manufacturer: Shield Line LLC
Category: otc | Type: HUMAN OTC DRUG LABEL
Date: 20161013

ACTIVE INGREDIENTS: LANOLIN 22 g/100 g
INACTIVE INGREDIENTS: ALUMINUM HYDROXIDE; .ALPHA.-TOCOPHEROL ACETATE; CALCIUM CARBONATE; CHOLECALCIFEROL; CITRIC ACID MONOHYDRATE; CORN OIL; ETHYLPARABEN; LANOLIN ALCOHOLS; MAGNESIUM HYDROXIDE; METHYLPARABEN; SODIUM CHLORIDE; SODIUM LAURETH SULFATE; PETROLATUM; VITAMIN A PALMITATE; WATER; ZINC CHLORIDE

DRUG FACTS

Active Ingredient

Lanolin 22%

Purpose

Skin Protectant

Uses

■ Helps prevent and temporarily protects chafed, chapped, or cracked skin

■ Temporarily protects minor: ■ cuts ■ cuts ■ scrapes ■ burns

Warnings

FOR EXTERNAL USE ONLY

When using this product

■ Avoid contact with eyes ■ If eye contact occurs, flush with water

Stop use and ask a doctor if

■ condition worsens

■ symptoms last more than seven days or clear up and occur again within several days

Do not use on

■ deep or puncture wounds

■ lacerations ■ animal bites

■ serious burns

Keep out of reach of children

If swallowed, get medical help or contact a Poison Control Center right away.

Directions

Apply as needed to clean skin twice daily or more often if necessary ■ For children under 6 months ask a doctor

Inactive Ingredients

Aluminum Hydroxide, Alpha Tocopherol Acetate (Vitamin E), Calcium Carbonate, Cholecalciferol (Vitamin D3), Citric Acid, Corn Oil, Ethylparaben, Lanolin Alcohols, Magnesium Hydroxide, Methylparaben, Sodium Chloride, Sodium Laureth Sulfate, Petrolatum, Vitamin A Palmitate, Water, Zinc Chloride